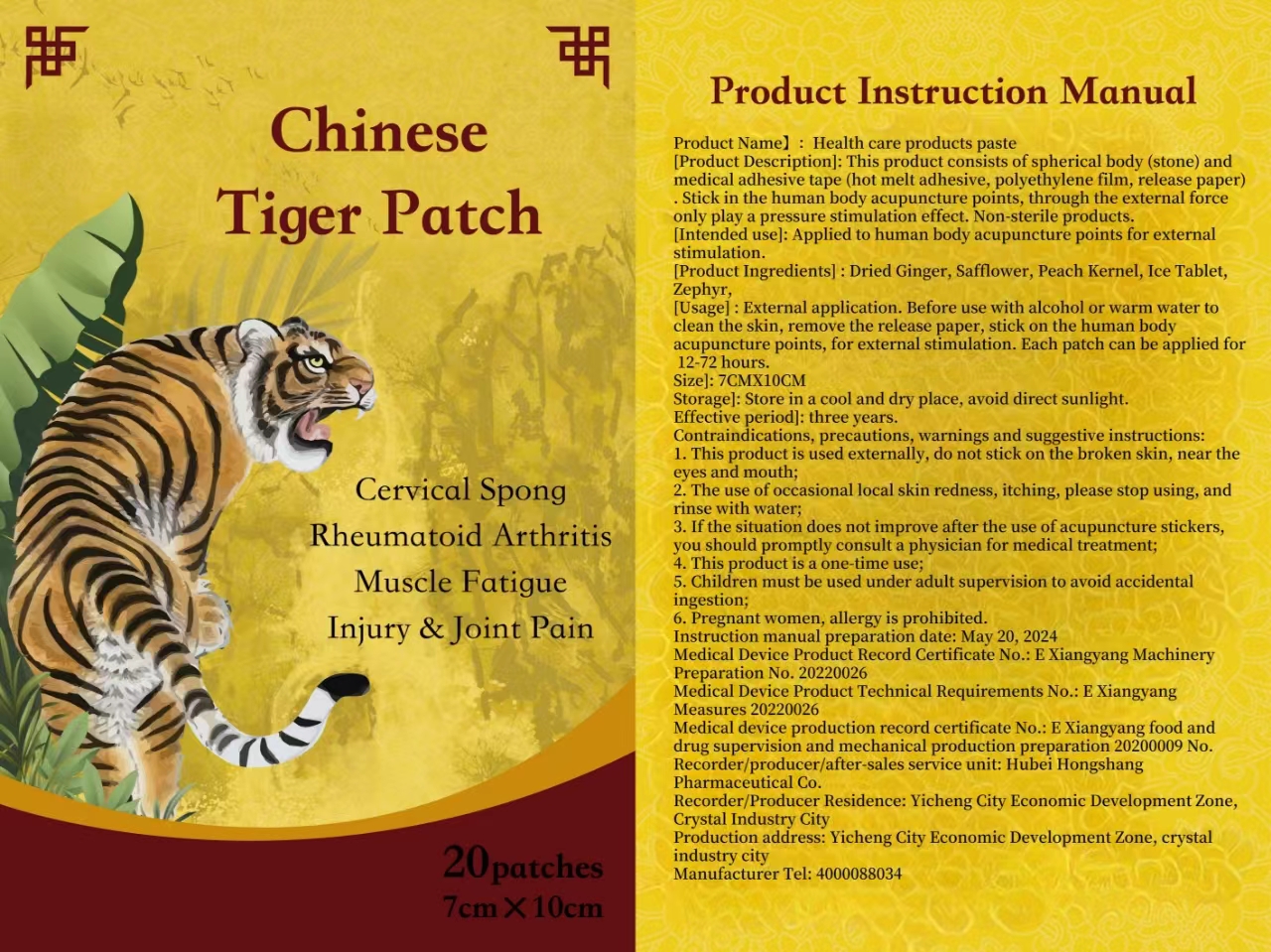 DRUG LABEL: HealthCareProductsPaste
NDC: 84372-017 | Form: PATCH
Manufacturer: Shenzhen Zhumeng Times Technology Co., Ltd.
Category: otc | Type: HUMAN OTC DRUG LABEL
Date: 20240824

ACTIVE INGREDIENTS: SAFFLOWER 1 g/20 a
INACTIVE INGREDIENTS: ABAMECTIN; GINGER; BORNEOL; PERSIC OIL

Active ingredients

Dried Ginger

Purpose

This product consists of a spherical body (stone) and medical adhesive tape (hot melt adhesive, polyethylene film, release paper). It is applied to acupuncture points on the human body and provides pressure stimulation through external force. This is a non-sterile product.

Uses

External application. Before use, clean the skin with alcohol or warm water, remove the release paper, and apply to acupuncture points on the human body for external stimulation. Each patch can be used for 12-72 hours.

Contraindications, Precautions, Warnings, and Instructions

1. This product is for external use only, do not apply to broken skin, near the eyes and mouth;<br>2. Occasionally, local skin redness and itching may occur during use, please stop using and rinse with water;<br>3. If the condition does not improve after using the acupuncture stickers, you should promptly consult a physician for medical treatment;<br>4. This product is for single-use only;<br>5. Children must be used under adult supervision to avoid accidental ingestion;<br>6. Pregnant women and those who are allergic are prohibited from using this product.

Dosage and administration

For external use only.

Do not use

Please make sure your skin is clean before use. Avoid using on open wounds or skin with allergic reactions.

When using section

External application. Before use, clean the skin with alcohol or warm water, remove the release paper, and apply to acupuncture points on the human body for external stimulation. Each patch can be used for 12-72 hours.

Inactive ingredients

Glycerin

stop use

Do not use on open wounds or allergic skin.

Keep out of reach of children.

If sxralowed, get medical help or contact a Poison Conirol Cenler ngiht away.

Inactive ingredients

Dried Ginger，Peach Kernel，Ice Tablet，Zephyr